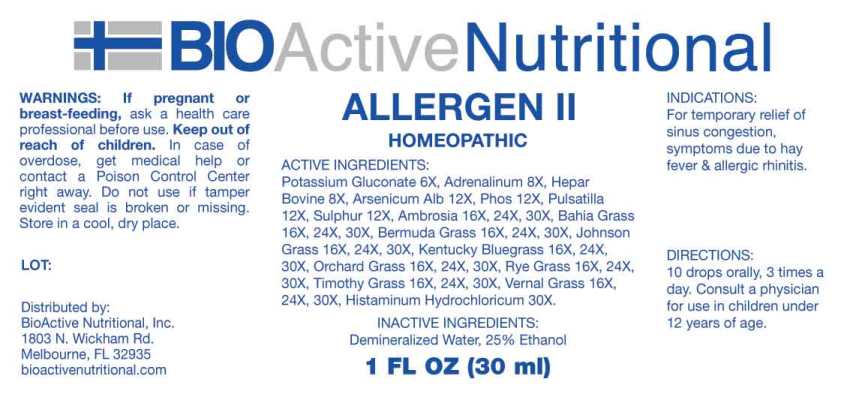 DRUG LABEL: Allergen
NDC: 43857-0557 | Form: LIQUID
Manufacturer: BioActive Nutritional, Inc.
Category: homeopathic | Type: HUMAN OTC DRUG LABEL
Date: 20230605

ACTIVE INGREDIENTS: POTASSIUM GLUCONATE 6 [hp_X]/1 mL; EPINEPHRINE 8 [hp_X]/1 mL; BEEF LIVER 8 [hp_X]/1 mL; ARSENIC TRIOXIDE 12 [hp_X]/1 mL; PHOSPHORUS 12 [hp_X]/1 mL; PULSATILLA PRATENSIS WHOLE 12 [hp_X]/1 mL; SULFUR 12 [hp_X]/1 mL; AMBROSIA ARTEMISIIFOLIA WHOLE 16 [hp_X]/1 mL; POA PRATENSIS TOP 16 [hp_X]/1 mL; DACTYLIS GLOMERATA TOP 16 [hp_X]/1 mL; CYNODON DACTYLON POLLEN 16 [hp_X]/1 mL; SORGHUM HALEPENSE POLLEN 16 [hp_X]/1 mL; LOLIUM PERENNE POLLEN 16 [hp_X]/1 mL; ANTHOXANTHUM ODORATUM 16 [hp_X]/1 mL; PASPALUM NOTATUM POLLEN 16 [hp_X]/1 mL; PHLEUM PRATENSE TOP 16 [hp_X]/1 mL; HISTAMINE DIHYDROCHLORIDE 30 [hp_X]/1 mL
INACTIVE INGREDIENTS: WATER; ALCOHOL

Drug Facts:

ACTIVE INGREDIENTS:

Potassium Gluconate 6X, Adrenalinum 8X, Hepar Bovine 8X, Arsenicum Album 12X, Phosphorus 12X, Pulsatilla (Pratensis) 12X, Sulphur 12X, Ambrosia Artemisiaefolia 16X, 24X, 30X, Kentucky Bluegrass 16X, 24X, 30X, Orchard Grass 16X, 24X, 30X, Bermuda Grass 16X, 24X, 30X , Johnson Grass 16X, 24X, 30X, Rye Grass 16X, 24X, 30X, Vernal Grass 16X, 24X, 30X, Bahia Grass 16X, 24X, 30X, Timothy Grass 16X, 24X, 30X, Histaminum Hydrochloricum 30X.

INDICATIONS:

For temporary relief of sinus congestion, symptoms due to hay fever & allergic rhinitis.

WARNINGS:

If pregnant or breast-feeding, ask a health care professional before use.

Keep out of reach of children. In case of overdose, get medical help or contact a Poison Control Center right away.

Do not use if tamper evident seal is broken or missing.

Store in cool, dry place.

Keep out of reach of children. In case of overdose, get medical help or contact a Poison Control Center right away.

DIRECTIONS:

10 drops orally, 3 times a day. Consult a physician for use in children under 12 years of age.

INDICATIONS:

For temporary relief of sinus congestion, symptoms due to hay fever & allergic rhinitis.

INACTIVE INGREDIENTS:

Demineralized Water, 25% Ethanol

QUESTIONS:

Distributed by:
BioActive Nutritional, Inc.
1803 N. Wickham Rd.
Melbourne, FL 32935
bioactivenutritional.com

PACKAGE LABEL DISPLAY:

BIOActive Nutritional

ALLERGEN II

HOMEOPATHIC

1FL OZ (30 ml)